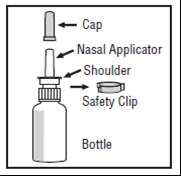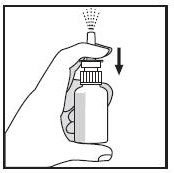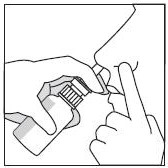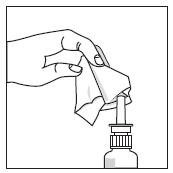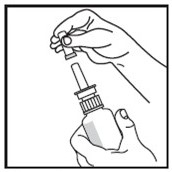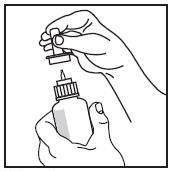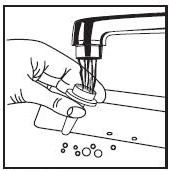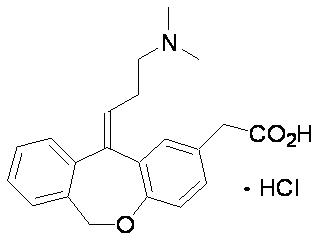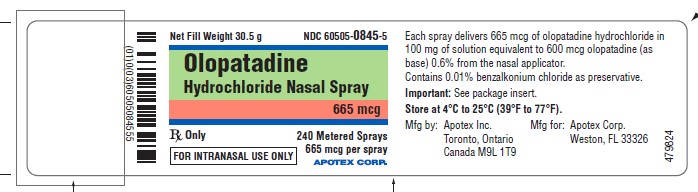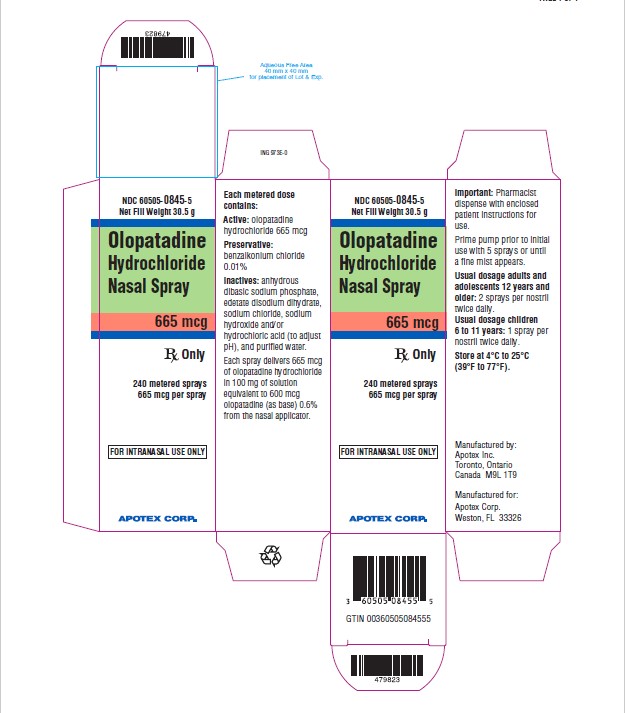 DRUG LABEL: Olopatadine Hydrochloride
NDC: 60505-0845 | Form: SPRAY, METERED
Manufacturer: Apotex Corp.
Category: prescription | Type: HUMAN PRESCRIPTION DRUG LABEL
Date: 20251105

ACTIVE INGREDIENTS: OLOPATADINE HYDROCHLORIDE  665 ug/1 1
INACTIVE INGREDIENTS: BENZALKONIUM CHLORIDE; SODIUM PHOSPHATE, DIBASIC, UNSPECIFIED FORM; EDETATE DISODIUM; SODIUM CHLORIDE; HYDROCHLORIC ACID; SODIUM HYDROXIDE; WATER

HIGHLIGHTS OF PRESCRIBING INFORMATION

These highlights do not include all the information needed to use OLOPATADINE HYDROCHLORIDE NASAL SPRAY safely and effectively. See full prescribing information for OLOPATADINE HYDROCHLORIDE NASAL SPRAY.
OLOPATADINE HYDROCHLORIDE nasal spray
Initial U.S. Approval: 1996

1 INDICATIONS AND USAGE

Olopatadine hydrochloride nasal spray is an H1 receptor antagonist indicated for the relief of the symptoms of seasonal allergic rhinitis in adults and pediatric patients 6 years of age and older (1).

2 DOSAGE AND ADMINISTRATION

For nasal use only.

Recommended dosages:

- Adults and Adolescents ≥12 Years: Two sprays per nostril (665 mcg per spray) twice daily (2.1).
- Pediatric Patients 6 to 11 Years: One spray per nostril (665 mcg per spray) twice daily (2.2).
- Priming Information: Prime olopatadine hydrochloride nasal spray before initial use and when olopatadine hydrochloride nasal spray has not been used for more than 7 days (2.3).

3 DOSAGE FORMS AND STRENGTHS

Nasal Spray: 665 mcg of olopatadine hydrochloride in each spray (3).

4 CONTRAINDICATIONS

None (4).

5 WARNINGS AND PRECAUTIONS

- Epistaxis, Nasal Ulceration, and Nasal Septal Perforation: Monitor patients periodically for signs of adverse effects on the nasal mucosa. Discontinue if ulcerations or perforations occur. Avoid use in patients with nasal disease other than allergic rhinitis (5.1).
- Avoid engaging in hazardous occupations requiring complete mental alertness and coordination, such as driving or operating machinery when taking olopatadine hydrochloride nasal spray (5.2).
- Avoid concurrent use of alcohol or other central nervous system depressants with olopatadine hydrochloride nasal spray (5.2).

6 ADVERSE REACTIONS

The most common (> 1%) adverse reactions, included bitter taste, headache, epistaxis, pharyngolaryngeal pain, post-nasal drip, cough, and urinary tract infection in patients 12 years of age and older and epistaxis, headache, upper respiratory tract infection, bitter taste, pyrexia, and rash in patients 6 to 11 years of age (6.1).

To report SUSPECTED ADVERSE REACTIONS, contact Apotex Corp. at 1-800-706-5575 or FDA at 1-800-FDA-1088 or www.fda.gov/medwatch.

FULL PRESCRIBING INFORMATION

1 INDICATIONS AND USAGE

Olopatadine hydrochloride nasal spray is indicated for the relief of the symptoms of seasonal allergic rhinitis in adults and pediatric patients 6 years of age and older.

2 DOSAGE AND ADMINISTRATION

2.1 Adults and Adolescents Twelve Years of Age and Older

The recommended dosage is two sprays per nostril twice daily.

2.2 Pediatric Patients Six to Eleven Years of Age

The recommended dosage is one spray per nostril twice daily.

2.3 Administration Information

Administer olopatadine hydrochloride nasal spray by the nasal route only.

Priming: Before initial use, prime olopatadine hydrochloride nasal spray by releasing 5 sprays or until a fine mist appears. The correct amount of medication cannot be assured before the initial priming.

Re-priming (as needed): When olopatadine hydrochloride nasal spray has not been used for more than 7 days, re-prime by releasing 2 sprays. Avoid spraying olopatadine hydrochloride nasal spray into the eyes.

Discard Instructions: Discard nasal device after 240 sprays (enough for 30 days of dosing) have been used even though the bottle is not completely empty. The correct amount of medication cannot be assured after 240 sprays have been used.

3 DOSAGE FORMS AND STRENGTHS

Nasal spray: 665 mcg olopatadine hydrochloride per spray supplied in a white plastic bottle with a metered-dose manual spray pump, a white nasal applicator, safety clip and a translucent overcap.

4 CONTRAINDICATIONS

None.

5 WARNINGS AND PRECAUTIONS

5.1 Local Nasal Effects

Epistaxis and Nasal Ulceration
In placebo-controlled clinical trials (vehicle nasal spray) of 2 weeks to 12 months duration, epistaxis and nasal ulcerations were reported [see Adverse Reactions (6.1)].

Nasal Septal Perforation
Three placebo-controlled long term (12 months) safety trials (vehicle nasal spray) were conducted. In the first safety trial, patients were treated with an investigational formulation of olopatadine hydrochloride nasal spray containing povidone (not the commercially marketed formulation) or a vehicle nasal spray containing povidone. Nasal septal perforations were reported in one patient treated with the investigational formulation of olopatadine hydrochloride nasal spray and 2 patients treated with the vehicle nasal spray. In the second safety trial with olopatadine hydrochloride nasal spray, which does not contain povidone, there were no reports of nasal septal perforation. In the third safety trial, one patient exposed to the 3.7 pH vehicle nasal spray (containing no povidone) reported a nasal septal perforation [see Adverse Reactions (6.1)].

Before starting olopatadine hydrochloride nasal spray, conduct a nasal examination to ensure that patients are free of nasal disease other than allergic rhinitis. Perform nasal examinations periodically for signs of adverse effects on the nasal mucosa and consider stopping olopatadine hydrochloride nasal spray if patients develop nasal ulcerations.

5.2 Somnolence and Impaired Mental Alertness

In clinical trials, the occurrence of somnolence has been reported in some patients taking olopatadine hydrochloride nasal spray [see Adverse Reactions (6.1)]. Patients should be cautioned against engaging in hazardous occupations requiring complete mental alertness and motor coordination, such as driving or operating machinery after administration of olopatadine hydrochloride nasal spray. Concurrent use of olopatadine hydrochloride nasal spray with alcohol or other central nervous system depressants should be avoided because additional reductions in alertness and additional impairment of central nervous system performance may occur.

6 ADVERSE REACTIONS

The most clinically significant adverse reactions described in other sections of labeling include:

- Epistaxis, Nasal Ulceration, and Nasal Septal Perforation [see Warnings and Precautions (5.1)]
- Somnolence and Impaired Mental Alertness [see Warnings and Precautions (5.2)]

6.1 Clinical Trials Experience

Because clinical trials are conducted under widely varying conditions, adverse reaction rates observed in the clinical trials of a drug cannot be directly compared to rates in the clinical trials of another drug and may not reflect the rates observed in practice.

The safety data described below reflect exposure to olopatadine hydrochloride nasal spray in 2,770 patients with seasonal or perennial allergic rhinitis in 10 controlled clinical trials of 2 weeks to 12 months duration. Olopatadine hydrochloride nasal spray is not indicated for use in patients with perennial allergic rhinitis.

The safety data from adults and adolescents are based upon 6 placebo-controlled clinical trials (3.7 pH vehicle nasal spray or 7.0 pH vehicle nasal spray) in which 1,834 patients with seasonal or perennial allergic rhinitis (652 males and 1,182 females) 12 years of age and older were treated with olopatadine hydrochloride nasal spray two sprays per nostril twice daily. There were 1,180 patients (olopatadine hydrochloride nasal spray, 587; vehicle nasal spray, 593) that participated in 3 efficacy and safety trials of 2 weeks duration. There were 2,840 patients (olopatadine hydrochloride nasal spray, 1,247; 3.7 pH vehicle nasal spray, 1,251; 7.0 pH vehicle nasal spray, 342) that participated in 3 long-term clinical trials of 1-year duration. The racial distribution of adult and adolescent patients receiving olopatadine hydrochloride nasal spray was 77% white, 9% black, and 14% other. The incidence of discontinuation due to adverse reactions in these controlled clinical trials was comparable for olopatadine hydrochloride nasal spray and vehicle nasal spray. Overall, 4.7% of the 1,834 adult and adolescent patients across all 6 studies treated with olopatadine hydrochloride nasal spray, 3.5% of the 1,844 patients treated with 3.7 pH vehicle nasal spray discontinued due to adverse reactions, and 2.9% of the 342 patients treated with 7.0 pH vehicle nasal spray discontinued due to adverse reactions.

The safety data from pediatric patients 6 to 11 years of age are based upon 3 clinical trials in which 870 children with seasonal allergic rhinitis (376 females and 494 males) were treated with olopatadine hydrochloride nasal spray one or two sprays per nostril twice daily for 2 weeks. The racial distribution of pediatric patients receiving olopatadine hydrochloride nasal spray was 68.6% white, 16.6% black, and 14.8% other. The incidence of discontinuation due to adverse reactions in these controlled clinical trials was comparable for olopatadine hydrochloride nasal spray and vehicle nasal spray. Overall, 1.4% of the 870 pediatric patients across all 3 studies treated with olopatadine hydrochloride nasal spray and 1.3% of the 872 pediatric patients treated with vehicle nasal spray discontinued due to adverse reactions.

Adults and Adolescents 12 Years of Age and Older in Short-Term (2 week) Trials

There were 1,180 patients 12 years of age and older (olopatadine hydrochloride nasal spray, 587; vehicle nasal spray, 593) that participated in 3 efficacy and safety trials of 2 weeks duration. Table 1 presents the most common adverse reactions (0.9% or greater in patients treated with olopatadine hydrochloride nasal spray that occurred more frequently in patients treated with olopatadine hydrochloride nasal spray compared with vehicle nasal spray in the 3 clinical trials of 2 weeks duration.

Table 1: Adverse Reactions Occurring at an Incidence of 0.9% or Greater in Controlled Clinical Trials of 2 Weeks Duration With Olopatadine Hydrochloride Nasal Spray in Adolescent and Adult Patients 12 Years of Age and Older With Seasonal Allergic Rhinitis
 | Adult and Adolescent Patients 12 Years and Older
Adverse Reaction | Olopatadine Hydrochloride Nasal Spray N = 587 | Vehicle Nasal Spray N = 593
Bitter taste | 75 (12.8%) | 5 (0.8%)
Headache | 26 (4.4%) | 24 (4%)
Epistaxis | 19 (3.2%) | 10 (1.7%)
Pharyngolaryngeal Pain | 13 (2.2%) | 8 (1.3%)
Post-nasal drip | 9 (1.5%) | 5 (0.8%)
Cough | 8 (1.4%) | 3 (0.5%)
Urinary tract infection | 7 (1.2%) | 3 (0.5%)
CPK elevation | 5 (0.9%) | 2 (0.3%)
Dry mouth | 5 (0.9%) | 1 (0.2%)
Fatigue | 5 (0.9%) | 4 (0.7%)
Influenza | 5 (0.9%) | 1 (0.2%)
Nasopharyngitis | 5 (0.9%) | 4 (0.7%)
Somnolence | 5 (0.9%) | 2 (0.3%)
Throat irritation | 5 (0.9%) | 0 (0%)

There were no differences in the incidence of adverse reactions based on gender or race. Clinical trials did not include sufficient numbers of patients 65 years of age and older to determine whether they respond differently from younger subjects.

Pediatric Patients 6 to 11 Years of Age

There were 1,742 pediatric patients 6 to 11 years of age (olopatadine nasal spray, 870; vehicle nasal spray, 872) with seasonal allergic rhinitis that participated in 3 clinical trials of 2 weeks duration. Two of the studies used the investigational formulation of olopatadine nasal spray, and one of the studies used olopatadine hydrochloride nasal spray. One study evaluated the safety of olopatadine hydrochloride nasal spray at doses of one and two sprays per nostril twice daily in 1,188 patients, in which 298 were exposed to olopatadine hydrochloride nasal spray 1 spray, 296 were exposed to olopatadine hydrochloride nasal spray (nasal spray) 2 sprays, 297 were exposed to vehicle 1 spray, and 297 were exposed to vehicle 2 sprays twice daily for 2 weeks. Table 2 presents the most common adverse reactions (greater than 1% in pediatric patients 6 to 11 years of age treated with olopatadine hydrochloride nasal spray one spray per nostril) that occurred more frequently with olopatadine hydrochloride nasal spray compared with vehicle nasal spray.

Table 2. Adverse Reactions Occurring at an Incidence of Greater Than 1% in a Controlled Clinical Trial of 2 Weeks Duration With Olopatadine Hydrochloride Nasal Spray in Pediatric Patients 6 to 11 Years of Age With Seasonal Allergic Rhinitis
 | Pediatric Patients 6 to 11 Years of Age
Adverse Reaction | Olopatadine Hydrochloride Nasal Spray One Spray per Nostril N = 298 | Vehicle Nasal Spray One Spray per Nostril N = 297
Epistaxis | 17 (5.7%) | 11 (3.7%)
Headache | 13 (4.4%) | 11 (3.7%)
Upper respiratory tract infection | 8 (2.6%) | 0
Bitter taste | 3 (1%) | 0
Pyrexia | 4 (1.3%) | 3 (1%)
Rash | 4 (1.3%) | 0

There were no differences in the incidence of adverse reactions based on gender, race, or ethnicity.

Long-Term (12 month) Safety Trials

In a 12-month, placebo-controlled, safety trial (vehicle nasal spray), 890 patients 12 years of age and older with perennial allergic rhinitis were randomized to treatment with olopatadine hydrochloride nasal spray two sprays per nostril twice daily (445 patients) or vehicle nasal spray (445 patients). In the olopatadine hydrochloride nasal spray and vehicle nasal spray groups, 72% and 74% of patients, respectively, completed the trial. Overall, 7% and 5%, respectively, discontinued study participation due to an adverse reaction. The most frequently reported adverse reaction was epistaxis, which occurred in 25% of patients treated with olopatadine hydrochloride nasal spray and 28% in patients treated with vehicle nasal spray. Epistaxis resulted in discontinuation of 0.9% of patients treated with olopatadine hydrochloride nasal spray and 0.2% of patients treated with vehicle nasal spray. Nasal ulcerations occurred in 10% of patients treated with olopatadine hydrochloride nasal spray and 9% of patients treated with vehicle nasal spray. Nasal ulcerations resulted in discontinuation of 0.4% of patients treated with olopatadine hydrochloride nasal spray and 0.2% patients treated with vehicle nasal spray. There were no patients with nasal septal perforation in either treatment group. Somnolence was reported in 1 patient treated with olopatadine hydrochloride nasal spray and 1 patient treated with vehicle nasal spray. Weight increase was reported in 6 patients treated with olopatadine hydrochloride nasal spray and 1 patient treated with vehicle nasal spray. Depression or worsening of depression occurred in 9 patients treated with olopatadine hydrochloride nasal spray and in 5 patients treated with vehicle nasal spray. Three patients, 2 of whom had preexisting histories of depression, who received olopatadine hydrochloride nasal spray were hospitalized for depression compared to none who received vehicle nasal spray.

In a second 12-month placebo-controlled, safety trial (vehicle nasal spray), 459 patients 12 years of age and older with perennial allergic rhinitis were treated with two sprays per nostril of an investigational formulation of olopatadine hydrochloride nasal spray containing povidone (not the commercially marketed formulation) and 465 patients were treated with 2 sprays of a vehicle nasal spray containing povidone. Nasal septal perforations were reported in one patient treated with the investigational formulation of olopatadine hydrochloride nasal spray and 2 patients treated with the vehicle nasal spray. Epistaxis was reported in 19% of patients treated with the investigational formulation of olopatadine hydrochloride nasal spray and 12% of patients treated with vehicle nasal spray. Somnolence was reported in 3 patients treated with the investigational formulation of olopatadine hydrochloride nasal spray compared to 1 patient treated with vehicle nasal spray. Fatigue was reported in 5 patients treated with the investigational formulation of olopatadine hydrochloride nasal spray compared to 1 patient treated with vehicle nasal spray.

In a third 3-arm, 12-month, placebo-controlled, safety trial (vehicle nasal spray), conducted post approval, 1,026 patients 12 years of age and older with perennial allergic rhinitis were randomized to treatment with olopatadine hydrochloride nasal spray (343 patients), a 3.7 pH vehicle nasal spray (341 patients), or a 7.0 pH vehicle nasal spray (342 patients). All treatments were administered as two sprays per nostril, twice daily. Overall, 5% of olopatadine hydrochloride nasal spray patients, 2% of 3.7 pH vehicle patients and 3% of 7.0 pH vehicle patients discontinued due to adverse reactions. The most frequently reported adverse reaction was epistaxis, which occurred in 24% of patients treated with olopatadine hydrochloride nasal spray, 20% of patients treated with 3.7 pH vehicle nasal spray, and 23% of patients treated with 7.0 pH vehicle nasal spray. Epistaxis resulted in the discontinuation of 2 patients treated with olopatadine hydrochloride nasal spray and 1 patient treated with 7.0 pH vehicle nasal spray. Nasal septal perforation was reported for one patient treated with the 3.7 pH vehicle nasal spray. Nasal ulcerations occurred in 9% of patients treated with olopatadine hydrochloride nasal spray, 8% of patients treated with 3.7 pH vehicle nasal spray, and 9% of patients treated with 7.0 pH vehicle nasal spray. Nasal ulceration resulted in the discontinuation of 1 patient treated with olopatadine hydrochloride nasal spray. Hyposmia and anosmia were each reported by one patient treated with olopatadine hydrochloride nasal spray. Neither somnolence nor weight loss was reported. Depression occurred in 3 patients treated with olopatadine hydrochloride nasal spray, 2 patients treated with 3.7 pH vehicle nasal spray, and 3 patients treated with 7.0 pH vehicle nasal spray.

There were no long-term clinical trials in children below 12 years of age.

6.2 Postmarketing Experience

During the post approval use of olopatadine hydrochloride nasal spray, the following adverse reactions have been identified. Because these reactions are reported voluntarily from a population of uncertain size, it is not always possible to reliably estimate their frequency or establish a causal relationship to drug exposure. The most common adverse reactions reported include dizziness, dysgeusia, epistaxis, headache, nasal discomfort, oropharyngeal pain, and somnolence. Additionally, hyposmia and anosmia have been reported with the use of olopatadine hydrochloride nasal spray.

7 DRUG INTERACTIONS

Formal drug-drug interaction studies were not conducted for olopatadine hydrochloride nasal spray. Drug interactions with inhibitors of liver enzymes are not anticipated because olopatadine is eliminated predominantly by renal excretion. Drug interactions involving P450 inhibition and plasma protein binding are also not expected [see Clinical Pharmacology (12.3)].

8 USE IN SPECIFIC POPULATIONS

8.1 Pregnancy

Risk Summary

Published data from postmarketing experience with antihistamines, with similar mechanism of action to olopatadine hydrochloride nasal spray, have not identified a drug-associated risk of major birth defects, miscarriage, or adverse maternal or fetal outcomes.

However, there are no published human data specific to olopatadine hydrochloride nasal spray. In animal reproductive studies, oral administration of olopatadine hydrochloride to pregnant rats and rabbits caused a decrease in the number of live fetuses at maternal doses approximately 110 and 1460 times the maximum recommended human daily intranasal dose (MRHDID) on a mg/m^2 basis, respectively (see Data).

The estimated background risk of major birth defects and miscarriage for the indicated population is unknown. All pregnancies have a background risk of birth defect, loss or other adverse outcomes. In the U.S. general population, the background risk of major birth defects and miscarriage in clinically recognized pregnancies is 2% to 4%, and 15% to 20%, respectively.

Data

Animal Data

In an oral embryo-fetal development study, pregnant rabbits were dosed throughout the period of organogenesis at doses up to 400 mg/kg/day. A decrease in the number of live fetuses was observed at 400 mg/kg/day (1460 times the MRHDID, on a mg/m^2 basis).

In an oral embryo-fetal development study, pregnant rats were dosed throughout the period of organogenesis at doses up to 600 mg/kg/day. Maternal toxicity, producing death and reduced maternal body weight gain was observed at 600 mg/kg/day (approximately 1100 times the MRHDID on a mg/m^2 basis). Olopatadine produced cleft palate at 60 mg/kg/day (approximately 110 times the MRHDID on a mg/m^2 basis) and decreased embryo-fetal viability and reduced fetal weight in rats at 600 mg/kg/day (approximately 1100 times the MRHDID on a mg/m^2 basis).

In peri-/postnatal toxicity studies, pregnant rats received oral doses of olopatadine up to 600 mg/kg/day during late gestation and throughout the lactation period. Olopatadine produced decreased neonatal survival at 60 mg/kg/day (approximately 110 times the MRHDID on a mg/m^2 basis) and reduced body weight gain in pups at 4 mg/kg/day (approximately 7 times the MRHDID on a mg/m^2 basis). These effects appeared attributable to exposure of pups via the milk as demonstrated in a cross-fostered study in which pups of untreated dams cross-fostered to dams treated with 60 mg/kg/day olopatadine orally during the lactation period exhibited decreased body weight gain.

8.2 Lactation

Risk Summary

There are no data on the presence of olopatadine in human milk, the effects on the breastfed infant, or the effects on milk production. Although orally administered olopatadine is present in rat milk, there is no information about nasally administered olopatadine.

It is not known whether topical nasal administration could result in sufficient systemic absorption to produce detectable quantities in human breast milk.

The developmental and health benefits of breastfeeding should be considered along with the mother’s clinical need for olopatadine hydrochloride nasal spray and any potential adverse effects on the breast fed infant from olopatadine hydrochloride nasal spray or from the underlying maternal condition.

8.4 Pediatric Use

The safety and effectiveness of olopatadine hydrochloride nasal spray for the relief of symptoms of seasonal allergic rhinitis have been established in pediatric patients aged 6 years and older.

The safety and effectiveness of olopatadine in pediatric patients 6 to 11 years of age are supported by 3 vehicle-controlled 2-week studies in 870 patients [see Adverse Reactions (6.1)]. Doses studied included one and two sprays per nostril twice daily. One of these studies evaluated the safety of olopatadine hydrochloride nasal spray at doses of one and two sprays per nostril twice daily in 1,188 patients, of which 298 patients were exposed to olopatadine hydrochloride nasal spray 1 spray, and 297 patients were exposed to vehicle 1 spray. In this study, the incidence of epistaxis with olopatadine hydrochloride nasal spray use was 5.7% [see Adverse Reactions (6.1), Clinical Studies (14)].

The safety and effectiveness of olopatadine hydrochloride nasal spray in pediatric patients aged 12 years and older are supported by 3 randomized, double blind, parallel group, multicenter, placebo-controlled clinical trials of 2 weeks duration in adult and adolescent patients [see Clinical Studies (14)]. In these studies, the incidence of epistaxis with olopatadine hydrochloride nasal spray use in 587 patients was 3.2% [see Adverse Reactions (6.1)].

The safety and effectiveness of olopatadine hydrochloride nasal spray have not been established in pediatric patients under 6 years of age.

The safety of olopatadine hydrochloride nasal spray at a dose of one spray per nostril twice daily was evaluated in one 2-week vehicle-controlled study in 132 pediatric patients 2 to 5 years of age with allergic rhinitis. In this trial, 66 patients were exposed to olopatadine hydrochloride nasal spray. The most common (greater than 1%) adverse reactions reported were diarrhea (9.1%), epistaxis (6.1%), rhinorrhea (4.5%), bitter taste (3%) and wheezing (3%). Diarrhea was reported more frequently (9.1%) in patients 2 to 5 years of age than 6 to 11 year old age group (< 1%).

8.5 Geriatric Use

Clinical studies of olopatadine hydrochloride nasal spray did not include sufficient numbers of patients aged 65 years and older to determine whether they respond differently from younger patients. Other reported clinical experience has not identified differences in responses between the elderly and younger patients. In general, dose selection for an elderly patient should be cautious, reflecting the greater frequency of decreased hepatic, renal, or cardiac function and of concomitant disease or other drug therapy.

10 OVERDOSAGE

Symptoms of antihistamine overdose may include drowsiness in both adults and children. Agitation and restlessness followed by drowsiness may also occur in children. There is no known specific antidote to olopatadine hydrochloride nasal spray. Should overdose occur, symptomatic or supportive treatment is recommended, taking into account any concomitantly ingested medications.

For additional information about overdose treatment, call a poison control center (1-800-222-1222).

11 DESCRIPTION

Olopatadine Hydrochloride Nasal Spray, 665 micrograms (mcg) is a metered-spray for nasal administration. Olopatadine hydrochloride, the active component of Olopatadine Hydrochloride Nasal Spray, is a white to off-white, water-soluble crystalline powder. The chemical name for olopatadine hydrochloride is (Z)-11-[3-(dimethylamino)propylidene]-6,11-dihydrodibenz[b,e] oxepin-2-acetic acid hydrochloride. It has a molecular weight of 373.88, and its molecular formula is C21H23NO3 • HCl with the following chemical structure:

Olopatadine Hydrochloride Nasal Spray contains 0.6% w/v olopatadine (base) in a nonsterile aqueous spray with pH of approximately 3.7. After initial priming (5 sprays), each metered spray from the nasal applicator delivers 100 microliters of the aqueous spray containing 665 mcg of olopatadine hydrochloride, which is equivalent to 600 mcg of olopatadine (base) [see Dosage Forms and Strengths (3)]. Olopatadine Hydrochloride Nasal Spray also contains anhydrous dibasic sodium phosphate, benzalkonium chloride (0.01%), edetate disodium dihydrate, sodium chloride, hydrochloric acid and/or sodium hydroxide (to adjust pH), and purified water.

12 CLINICAL PHARMACOLOGY

12.1 Mechanism of Action

Olopatadine is a histamine H1 receptor antagonist. The antihistaminic activity of olopatadine has been documented in isolated tissues, animal models, and humans.

12.2 Pharmacodynamics

Cardiac Electrophysiology
In a placebo-controlled cardiovascular safety study, 32 healthy volunteers received 20 mg oral spray of olopatadine twice daily for 14 days (8-fold greater daily dose than the recommended daily nasal dose). The mean QTcF (QT corrected by Fridericia's correction method for heart rate) change from baseline was -2.7 msec and -3.8 msec for olopatadine, and placebo, respectively. In this study, 8 subjects treated with olopatadine had a QTcF change from baseline of 30 to 60 msec, 1 subject had a QTcF change from baseline greater than 60 msec, and no subjects had QTcF values greater than 500 msec. Eight subjects treated with placebo had a QTcF change from baseline of 30 to 60 msec, no subjects had a QTcF change from baseline greater than 60 msec, and no subjects had QTcF values greater than 500 msec. In a 12-month study in 429 perennial allergic rhinitis patients treated with olopatadine hydrochloride nasal spray two sprays per nostril twice daily, no evidence of any effect of olopatadine hydrochloride on QT prolongation was observed.

12.3 Pharmacokinetics

The pharmacokinetic properties of olopatadine were studied after administration by the nasal, oral, intravenous, and topical ocular routes. Olopatadine exhibited linear pharmacokinetics across the routes studied over a large dose range.

Absorption
Healthy Subjects: Olopatadine was absorbed with individual peak plasma concentrations observed between 30 minutes and 1 hour after twice daily intranasal administration of olopatadine hydrochloride nasal spray. The mean (± SD) steady-state peak plasma concentration (Cmax) of olopatadine was 16 ± 8.99 ng/mL. Systemic exposure as indexed by area under the curve (AUC0-12) averaged 66 ± 26.8 ng·h/mL. The average absolute bioavailability of intranasal olopatadine is 57%. The mean accumulation ratio following multiple intranasal administration of olopatadine hydrochloride nasal spray was about 1.3.

Seasonal Allergic Rhinitis Patients: Systemic exposure of olopatadine in seasonal allergic rhinitis (SAR) patients after twice daily intranasal administration of olopatadine hydrochloride nasal spray was comparable to that observed in healthy subjects. Olopatadine was absorbed with peak plasma concentrations observed between 15 minutes and 2 hours. The mean steady-state Cmax was 23.3 ± 6.2 ng/mL and AUC0-12 averaged 78 ± 13.9 ng·h/mL.

Distribution
The protein binding of olopatadine was moderate at approximately 55% in human serum, and independent of drug concentration over the range of 0.1 to 1000 ng/mL. Olopatadine was bound predominately to human serum albumin.

Elimination

The plasma elimination half-life of olopatadine is 8 to 12 hours. Olopatadine is mainly eliminated through urinary excretion. Approximately 70% of a [^14C] olopatadine hydrochloride oral dose was recovered in urine with 17% in the feces. Of the drug-related material recovered within the first 24 hours in the urine, 86% was unchanged olopatadine with the balance comprised of olopatadine N-oxide and N-desmethyl olopatadine.

Metabolism
Olopatadine is not extensively metabolized. Based on plasma metabolite profiles following oral administration of [^14C] olopatadine, at least six minor metabolites circulate in human plasma. Olopatadine accounts for 77% of peak plasma total radioactivity and all metabolites amounted to <6% combined. Two of these have been identified as the olopatadine N-oxide and N-desmethyl olopatadine. In in vitro studies with cDNA-expressed human cytochrome P450 isoenzymes (CYP) and flavin-containing monooxygenases (FMO), N-desmethyl olopatadine (Ml) formation was catalyzed mainly by CYP3A4, while olopatadine N-oxide (M3) was primarily catalyzed by FMO1 and FMO3. Olopatadine at concentrations up to 33,900 ng/mL did not inhibit the in vitro metabolism of specific substrates for CYP1A2, CYP2C9, CYP2C19, CYP2D6, CYP2E1, and CYP3A4. The potential for olopatadine and its metabolites to act as inducers of CYP enzymes has not been evaluated.

Specific Populations

Patients with Hepatic Impairment
No specific pharmacokinetic study examining the effect of hepatic impairment was conducted. Since metabolism of olopatadine is a minor route of elimination, no adjustment of the dosing regimen of olopatadine hydrochloride nasal spray is warranted in patients with hepatic impairment.

Patients with Renal Impairment
The mean Cmax values for olopatadine following single nasal doses were not markedly different between healthy subjects (18.1 ng/mL) and patients with mild, moderate, and severe renal impairment (range 15.5 to 21.6 ng/mL). The mean plasma AUC0-12 was 2-fold higher in patients with severe impairment (creatinine clearance <30 mL/min/1.73 m^2). In these patients, peak steady-state plasma concentrations of olopatadine are approximately 10-fold lower than those observed after higher 20 mg oral doses, twice daily, which were well-tolerated. These findings indicate that no adjustment of the dosing regimen of olopatadine hydrochloride nasal spray is warranted in patients with renal impairment.

Male and Female Patients
The mean systemic exposure (Cmax and AUC0-12) in female SAR patients following multiple administration of olopatadine was 40% and 27% higher, respectively than those values observed in male SAR patients.

Racial or Ethnic Groups
The effects of race on olopatadine pharmacokinetics have not been adequately investigated.

Pediatric Patients 6 to 11 Years of Age

The systemic pharmacokinetics of olopatadine, olopatadine N-oxide and N-desmethyl olopatadine in patients 6 through 11 years of age were characterized using data from 42 pediatric patients administered olopatadine hydrochloride nasal spray, one spray per nostril twice daily for a minimum of 14 days. The mean Cmax (15.4 ± 7.3 ng/mL) of olopatadine was approximately 2-fold less than was comparable to that observed in adults (78 ± 13.9 ng·h/mL). The Cmax and AUC0-12 of olopatadine N-oxide were comparable to that observed in adults. The Cmax and AUC0-12 of N-desmethyl olopatadine are approximately 18% and 37% higher than that observed in adults, respectively.

Pediatric Patients 2 to 5 Years of Age

The systemic pharmacokinetics of olopatadine, olopatadine N-oxide, and N-desmethyl olopatadine were characterized using population pharmacokinetic methods applied to sparse data (approximately 5 samples per patient) obtained from 66 pediatric patients (2 to less than 6 years of age) administered one-half the recommended adult dose (one spray per nostril) of olopatadine hydrochloride nasal spray twice daily for a minimum of 14 days. The mean Cmax and AUC0-12 of olopatadine were 13.4 ± 4.6 ng/mL and 75 ± 26.4 ng.hr/mL respectively. The mean Cmax and AUC0-12 of olopatadine N-oxide and N-desmethyl olopatadine were similar to that of patients 6 to 11 years of age.

Drug Interaction Studies
Drug interactions with inhibitors of liver enzymes are not anticipated because olopatadine is eliminated predominantly by renal excretion. Olopatadine did not inhibit the in vitro metabolism of specific substrates for CYP1A2, CYP2C9, CYP2C19, CYP2D6, CYP2E1, and CYP3A4. Based on these data, drug interactions involving P450 inhibition are not expected. Due to the modest protein binding of olopatadine (55%), drug interactions through displacement from plasma proteins are also not expected.

13 NONCLINICAL TOXICOLOGY

13.1 Carcinogenesis, Mutagenesis, Impairment of Fertility

Carcinogenicity

Olopatadine demonstrated no tumorigenic potential in mice at oral doses up to 500 mg/kg/day (approximately 460 times the MRHDID on a mg/m^2 basis) for 78 weeks or in rats at oral doses up to 200 mg/kg/day (approximately 370 times the MRHDID on a mg/m^2 basis) for 104 weeks.

Mutagenesis

No mutagenic potential was observed when olopatadine was tested in an in vitro bacterial reverse mutation (Ames) test, an in vitro mammalian chromosome aberration assay or an in vivo mouse micronucleus test.

Impairment of Fertility

Olopatadine administered at an oral dose of 400 mg/kg/day, (approximately 730 times the MRHDID for adults on an mg/m^2 basis) produced toxicity in male and female rats, and resulted in a decrease in the fertility index and reduced implantation rate. No effects on reproductive function were observed at 50 mg/kg/day (approximately 90 times the MRHDID on a mg/m^2 basis).

14 CLINICAL STUDIES

Adult and Adolescent Patients 12 Years of Age and Older

The efficacy and safety of olopatadine hydrochloride nasal spray were evaluated in 3 randomized, double blind, parallel group, multicenter, placebo-controlled clinical trials (vehicle nasal spray) of 2 weeks duration in adult and adolescent patients, 12 years of age and older with symptoms of seasonal allergic rhinitis. The 3 clinical trials were conducted in the United States and included 1,598 patients (556 males, and 1,042 females) 12 years of age and older. In these 3 trials, 587 patients were treated with olopatadine hydrochloride nasal spray 0.6%, 418 patients were treated with olopatadine hydrochloride nasal spray 0.4% and 593 patients were treated with vehicle nasal spray. Assessment of efficacy was based on patient recording of 4 individual nasal symptoms (nasal congestion, rhinorrhea, itchy nose, and sneezing) on a 0 to 3 categorical severity scale (0 = absent, 1 = mild, 2 = moderate, 3 = severe) as reflective or instantaneous scores. Reflective scoring required patients to record symptom severity over the previous 12 hours; the instantaneous scoring required patients to record symptom severity at the time of recording. The primary efficacy endpoint was the difference from placebo in the percent change from baseline in the average of morning and evening reflective total nasal symptom score (rTNSS) averaged for the 2-week treatment period. In all 3 trials, patients treated with olopatadine hydrochloride nasal spray, two sprays per nostril, twice-daily, exhibited statistically significantly greater decreases in rTNSS compared to vehicle nasal spray. Results for the rTNSS from 2 representative trials are shown in Table 3.

Table 3: Mean Reflective Total Nasal Symptom Score (rTNSS) in Adult and Adolescent Patients With Seasonal Allergic Rhinitis
 |  |  |  | Change From | Difference From Placebo
Study No. | Treatment | N | Baseline | Baseline | Estimate | 95% CI | p-value
Study 1 | Olopatadine Hydrochloride Nasal Spray 0.6% | 183 | 8.71 | -3.63 | -0.96 | (-1.42, -0.51) | <0.0001
 | Olopatadine Hydrochloride Nasal Spray 0.4% | 188 | 8.90 | -3.38 | -0.71 | (-1.17, -0.26) | 0.0023
 | Vehicle Nasal Spray | 191 | 8.75 | -2.67
Study 2 | Olopatadine Hydrochloride Nasal Spray 0.6% | 220 | 9.17 | -2.90 | -0.98 | (-1.37, -0.59) | <0.0001
 | Olopatadine Hydrochloride Nasal Spray 0.4% | 228 | 9.26 | -2.63 | -0.72 | (-1.11, -0.33) | 0.0003
 | Vehicle Nasal Spray | 223 | 9.07 | -1.92

Abbreviation: CI, confidence interval.

Itchy eyes and watery eyes were evaluated as secondary endpoints but eye redness was not evaluated. In 2 of the studies, patients treated with olopatadine hydrochloride nasal spray had significantly greater decreases in reflective symptom scores for itchy eyes and watery eyes, compared to vehicle nasal spray.

In the 2-week seasonal allergy trials, onset of action was also evaluated by instantaneous TNSS assessments twice-daily after the first dose of study medication. In these trials, onset of action was seen after 1 day of dosing. Onset of action was evaluated in 3 environmental exposure unit studies with single doses of olopatadine hydrochloride nasal spray. In these studies, patients with seasonal allergic rhinitis were exposed to high levels of pollen in the environmental exposure unit and then treated with either olopatadine hydrochloride nasal spray or vehicle nasal spray, two sprays in each nostril, after which they self-reported their allergy symptoms hourly as instantaneous scores for the subsequent 12 hours. Olopatadine hydrochloride nasal spray 0.6% was found to have an onset of action of 30 minutes after dosing in the environmental exposure unit.

Pediatric Patients 6 to 11 Years of Age
There were 3 clinical trials of 2 weeks duration with olopatadine nasal spray in patients 6 to 11 years of age with seasonal allergic rhinitis. Efficacy of olopatadine hydrochloride nasal spray was evaluated in 2 of the 3 trials. One of the 2 trials that showed efficacy was a randomized, double blind, parallel group, multicenter, placebo (vehicle nasal spray)-controlled clinical trial of 2 weeks duration, including 1,188 children ages 6 to < 12 years with seasonal allergic rhinitis. Assessment of efficacy was based on patient/caregiver recording of 4 individual nasal symptoms (nasal congestion, rhinorrhea, itchy nose, and sneezing) on a 0 to 3 categorical severity scale (0 = absent, 1 = mild, 2 = moderate, 3 = severe) as reflective or instantaneous scores. Reflective scoring captured symptom severity over the previous 12 hours; the instantaneous scoring captured symptom severity at the time of recording. The primary efficacy endpoint was the difference from placebo in the percent change from baseline in the average of patient/caregiver-reported morning and evening reflective total nasal symptom score (rTNSS) averaged for the 2-week treatment period. Patients treated with olopatadine hydrochloride nasal spray, one or two sprays per nostril twice daily, had statistically significantly greater decreases in rTNSS compared to vehicle nasal spray. Results for rTNSS are shown in Table 4.

Table 4: Mean Reflective Total Nasal Symptom Score in Pediatric Patients 6 to 11 Years of Age with Seasonal Allergic Rhinitis
 |  |  | Change From | Difference from Placebo
Treatment | N | Baseline | Baseline | Estimate | 95% CI | p-value
Olopatadine Hydrochloride Nasal Spray 0.6%, one spray per nostril twice daily | 294 | 8.99 | - 2.24 | -0.55 | (-0.90, -0.19) | 0.0015
Vehicle Nasal Spray, one spray per nostril twice daily | 294 | 9.09 | -1.70

Abbreviation: CI, confidence interval.

Itchy eyes and watery eyes were evaluated as secondary endpoints in the same study but eye redness was not evaluated. Patients treated with olopatadine hydrochloride nasal spray had significantly greater decreases in reflective symptom scores for itchy eyes and watery eyes, compared to vehicle nasal spray.

16 HOW SUPPLIED/STORAGE AND HANDLING

How Supplied

Olopatadine hydrochloride nasal spray, 665 mcg is supplied in a white, opaque HDPE cylindrical bottle with a metered-dose spray pump, a white actuator, safety clip and a translucent overcap in a box of 1 (NDC 60505-0845-5). Each trade size bottle contains 30.5 g of clear, colorless liquid and will provide 240 metered sprays. After priming [see Dosage and Administration (2.3)], each spray delivers a fine mist containing 665 mcg of olopatadine hydrochloride in 100 microliters of formulation through the nozzle.

Net content 30.5 g, 240 sprays: NDC 60505-0845-5 (trade size)

Storage

Store olopatadine hydrochloride nasal spray at room temperature between 4°C to 25°C (39°F to 77°F).

17 PATIENT COUNSELING INFORMATION

Advise the patient to read the FDA-approved patient labeling (Patient Information and Instructions for Use).

Local Nasal Effects and Other Common Adverse Reactions

Inform patients that treatment with olopatadine hydrochloride nasal spray may lead to adverse reactions, which include epistaxis and nasal ulcerations [see Warnings and Precautions (5.1)]. Other common adverse reactions reported with use of olopatadine hydrochloride nasal spray include bitter taste, headache, and pharyngolaryngeal pain [see Adverse Reactions (6)].

Somnolence and Impaired Mental Alertness

Somnolence has been reported in some patients taking olopatadine hydrochloride nasal spray. Caution patients against engaging in hazardous occupations requiring complete mental alertness and motor coordination, such as driving or operating machinery after administration of olopatadine hydrochloride nasal spray [see Warnings and Precautions (5.2)].

Concurrent Use of Alcohol and Other Central Nervous System Depressants

Advise patients that concurrent use of olopatadine hydrochloride nasal spray with alcohol or other central nervous system depressants should be avoided because additional reductions in alertness and additional impairment of central nervous system performance may occur [see Warnings and Precautions (5.2)].

Keep Spray Out of Eyes

Inform patients to avoid spraying olopatadine hydrochloride nasal spray in their eyes [see Dosage and Administration (2.3)].

APOTEX INC.
OLOPATADINE HYDROCHLORIDE NASAL SPRAY

Manufactured by | Manufactured for
Apotex Inc. | Apotex Corp.
Toronto, Ontario | Weston, FL
Canada M9L 1T9 | 33326

Revision: 01

PATIENT INFORMATION

Olopatadine Hydrochloride
(OH-loe-PA-ta-deen HYE-droe-KLOR-ide)
Nasal Spray, for intranasal use

What is olopatadine hydrochloride nasal spray?

Olopatadine hydrochloride nasal spray is a prescription nasal spray that contains an antihistamine. Olopatadine hydrochloride nasal spray is used to treat seasonal allergy symptoms in adults and children 6 years of age and older. It is not known if olopatadine hydrochloride nasal spray is safe and effective in children under 6 years of age.

Before using olopatadine hydrochloride nasal spray, tell your healthcare provider about all of your medical conditions, including if you:

- have nose problems, such as nose bleeds, or sores in the nose.
- are pregnant or planning to become pregnant. It is not known if olopatadine hydrochloride nasal spray will harm your unborn baby.
- are breastfeeding or plan to breastfeed. It is not known if olopatadine hydrochloride nasal spray passes into your breast milk. You and your healthcare provider should decide if you will use olopatadine hydrochloride nasal spray if you plan to breastfeed.

Tell your healthcare provider about all the medicines you take, including prescription and over-the-counter medicines, vitamins, and herbal supplements.

Olopatadine hydrochloride nasal spray and other medicines may affect each other and cause side effects.

Know the medicines you take. Keep a list of your medicines and show it to your healthcare provider or pharmacist when you get a new medicine.

How should I use olopatadine hydrochloride nasal spray?

- See the “Instructions for Use” at the end of this Patient Information leaflet for information about the right way to use olopatadine hydrochloride nasal spray.
- Olopatadine hydrochloride nasal spray is for use in your nose only. Do not spray it in your eyes or mouth.
- Use olopatadine hydrochloride nasal spray exactly as your healthcare provider tells you to use it.
- Do not use more than your healthcare provider tells you.
- If you use too much olopatadine hydrochloride nasal spray, call your healthcare provider or pharmacist right away
- Throw away olopatadine hydrochloride nasal spray after 240 sprays (about 30 days) after the first priming. Even though the bottle may not be completely empty, you may not get the correct dose of medicine if you continue to use it.

What should I avoid while using olopatadine hydrochloride nasal spray?

- Olopatadine hydrochloride nasal spray can cause sleepiness or drowsiness. Do not drive, operate machinery, or do anything that needs you to be alert until you know how olopatadine hydrochloride nasal spray affects you.
- Do not drink alcohol or take any medicines that may cause you to feel sleepy while using olopatadine hydrochloride nasal spray. It may make your sleepiness worse.

What are the possible side effects of olopatadine hydrochloride nasal spray?

Olopatadine hydrochloride nasal spray may cause serious side effects, including:

- nosebleeds.
- sores in the nose.
- hole in the cartilage between the nose (nasal septum perforation). A whistling sound when you breathe may be a symptom of nasal septum perforation.
- sleepiness or drowsiness.

The most common side effects of olopatadine hydrochloride nasal spray in people 12 years of age and older include:

- bad or bitter taste

- throat pain

- cough

- headache

- nose congestion

- urinary tract infection

The most common side effects of olopatadine hydrochloride nasal spray in people 6 to 11 years of age include:

- headache

- bad or bitter taste

- rash

- upper respiratory tract infection

- fever

Tell your healthcare provider if you have any side effect that bothers you or that does not go away.

These are not all of the possible side effects of olopatadine hydrochloride nasal spray. For more information, ask your healthcare provider or pharmacist.

Call your doctor for medical advice about side effects. You may report side effects to FDA at 1-800-FDA-1088.

How should I store olopatadine hydrochloride nasal spray?

- Store olopatadine hydrochloride nasal spray at room temperature between 39°F to 77°F (4°C to 25°C).
- Do not use your olopatadine hydrochloride nasal spray after the expiration date on the label or box.

Keep olopatadine hydrochloride nasal spray and all medicines out of the reach of children.

General information about olopatadine hydrochloride nasal spray.

Medicines are sometimes prescribed for conditions that are not mentioned in the Patient Information leaflet. Do not use olopatadine hydrochloride nasal spray for a condition for which it was not prescribed. Do not give olopatadine hydrochloride nasal spray to other people, even if they have the same symptoms you have. It may harm them. You can ask your healthcare provider or pharmacist for information about olopatadine hydrochloride nasal spray that is written for health professionals.

What are the ingredients of Olopatadine Hydrochloride Nasal Spray?

Active ingredient: olopatadine hydrochloride 665 micrograms per spray.

Inactive ingredients: anhydrous dibasic sodium phosphate, benzalkonium chloride (0.01%), edetate disodium dihydrate, sodium chloride, hydrochloric acid and/or sodium hydroxide and purified water.

APOTEX INC.
OLOPATADINE HYDROCHLORIDE NASAL SPRAY

Manufactured by | Manufactured for
Apotex Inc. | Apotex Corp.
Toronto, Ontario | Weston, FL
Canada M9L 1T9 | 33326

Revision: 01

Revised: November 2025

PATIENT INFORMATION

INSTRUCTIONS FOR USE

Olopatadine Hydrochloride

(OH-loe-PA-ta-deen HYE-droe-KLOR-ide)

nasal spray, for intranasal use

This Instructions for Use contains information on how to use olopatadine hydrochloride nasal spray.

Read this Instructions for Use that comes with olopatadine hydrochloride nasal spray before you start using it and each time you get a refill. There may be new information. This information does not take the place of talking with your healthcare provider about your medical condition or treatment.

Olopatadine hydrochloride nasal spray is for use in your nose only. Do not spray olopatadine hydrochloride nasal spray in your eyes or mouth.

Important information you need to know before using olopatadine hydrochloride nasal spray

- Use olopatadine hydrochloride nasal spray exactly how your healthcare provider tells you to use it.
- Your olopatadine hydrochloride nasal spray bottle must be shaken and primed before you use it for the first time and when you have not used it for more than 7 days.
- Throw away olopatadine hydrochloride nasal spray after 240 sprays after the first priming. Even though the bottle may not be completely empty, you may not get the correct dose of medicine if you continue to use it.

Using olopatadine hydrochloride nasal spray

Step 1. Remove the plastic cap (see Figure A).

Figure A

Step 2. Hold the bottle and press down on the shoulders of the nasal applicator with your forefinger and middle finger.

- Support the bottom of the bottle with your thumb (see Figure B). Prime the bottle by pressing and releasing the shoulders of the bottle down firmly 5 times or until you see a fine mist come out of the nasal applicator.
- Now your pump is primed and ready to use.
- If you do not use olopatadine hydrochloride nasal spray for more than 7 days, you will need to prime the bottle again by pressing and releasing the shoulders of the bottle down firmly 2 times or until you see a fine mist come out of the nasal applicator.
  Figure B

Step 3. Gently blow your nose to clear your nostrils. Hold 1 nostril closed with a finger. Tilt your head down (chin toward chest) and insert the nasal applicator into a nostril. Hold the bottle upright with the nasal applicator tip pointing away from the center of the nose (see Figure C).

Step 4. Breathe in gently through your nose. While breathing in, press firmly and quickly on the nasal applicator shoulders to release the spray into your nostril (see Figure C).

Figure C

Step 5. Breathe out through your mouth. Do not tilt your head back or blow your nose right after using olopatadine hydrochloride nasal spray. This may cause you to get a bitter taste in your mouth.

Step 6. Repeat Steps 3 through 5 above to deliver a spray in your other nostril.

Step 7. If your healthcare provider tells you to use 2 sprays in each nostril, repeat Steps 3 through 5 for the second spray in each nostril.

Step 8. Wipe the nasal applicator with a clean tissue and replace the plastic cap (see Figure D).

Figure D

Cleaning the olopatadine hydrochloride nasal spray nasal applicator

Step 9. To clean the nasal applicator, remove the plastic cap (see Figure E).

If the nasal applicator becomes clogged, do not try to clear it using a pointed object.

Figure E

Step 10. Gently pull the nasal applicator up to remove it from the bottle (see Figure F).

Figure F

Step 11. With the nasal applicator pointing downwards, wash it by running warm tap water into the nasal applicator for about 1 minute (see Figure G).

Step 12. Shake the nasal applicator to remove any water and put the nasal applicator back on the bottle.

Step 13. Prime the bottle again by pressing the shoulders of the bottle down firmly and releasing the shoulders 2 times or until you see a fine mist come out of the white nasal applicator. Repeat Steps 11 and 12 above if the nasal applicator is still clogged.

Figure G

How should I store olopatadine hydrochloride nasal spray?

- Store olopatadine hydrochloride nasal spray at room temperature between 39°F to 77°F (4°C to 25°C).
- Do not use olopatadine hydrochloride nasal spray after the expiration date on the label or box.

Keep olopatadine hydrochloride nasal spray and all medicines out of the reach of children.

For more information about olopatadine hydrochloride nasal spray visit www.apotex.com or call 1-800-706-5575.

APOTEX INC.

OLOPATADINE HYDROCHLORIDE NASAL SPRAY

Manufactured by | Manufactured for
Apotex Inc. | Apotex Corp
Toronto, Ontario | Weston, FL
Canada M9L 1T9 | 33326

Revised: November 2025

PACKAGE LABEL

PRINCIPAL DISPLAY PANEL - Bottle

Olopatadine Hydrochloride Nasal Spray 665 mcg

FOR INTRANASAL USE ONLY

Rx Only

240 Metered Sprays

Net Fill Weight 30.5g

Apotex Corp.

NDC 60505-0845-5

PACKAGE LABEL

PRINCIPAL DISPLAY PANEL - Carton

Olpatadine Hydrochloride Nasal Spray, 665mcg

FOR INTRANASAL USE ONLY

Rx Only

240 Metered Sprays

Net Fill Weight 30.5g

Apotex Corp.

NDC 60505-0845-5